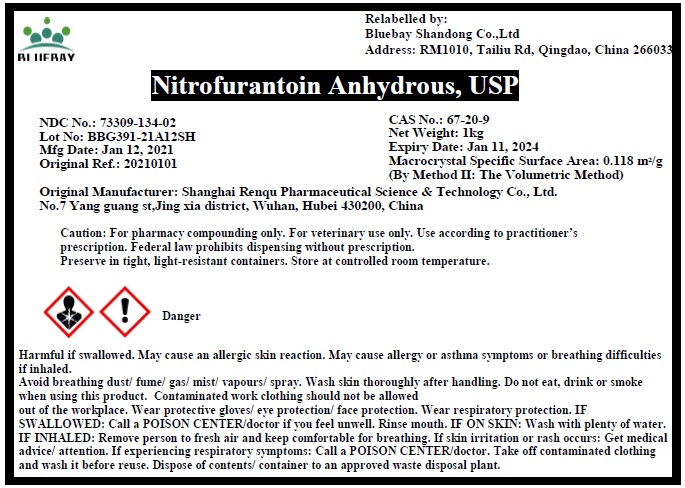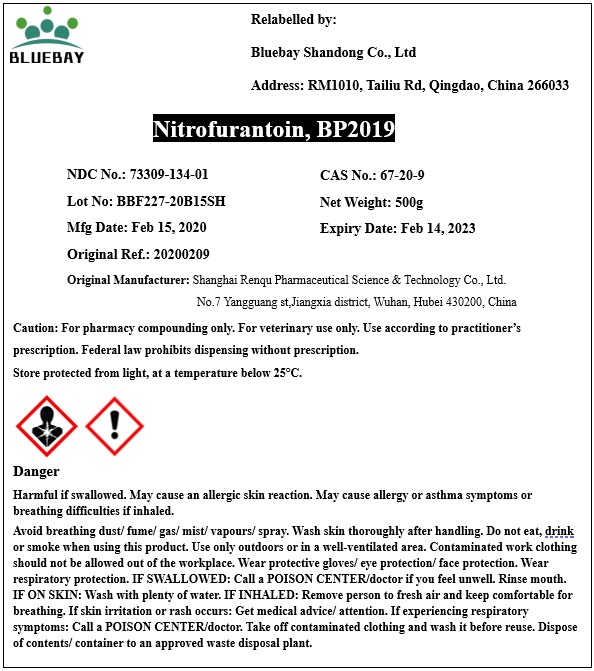 DRUG LABEL: Nitrofurantoin
NDC: 73309-134 | Form: POWDER
Manufacturer: BLUEBAY SHANDONG CO.,LTD
Category: other | Type: BULK INGREDIENT
Date: 20210803

ACTIVE INGREDIENTS: NITROFURANTOIN 1 g/1 g

Nitrofurantoin